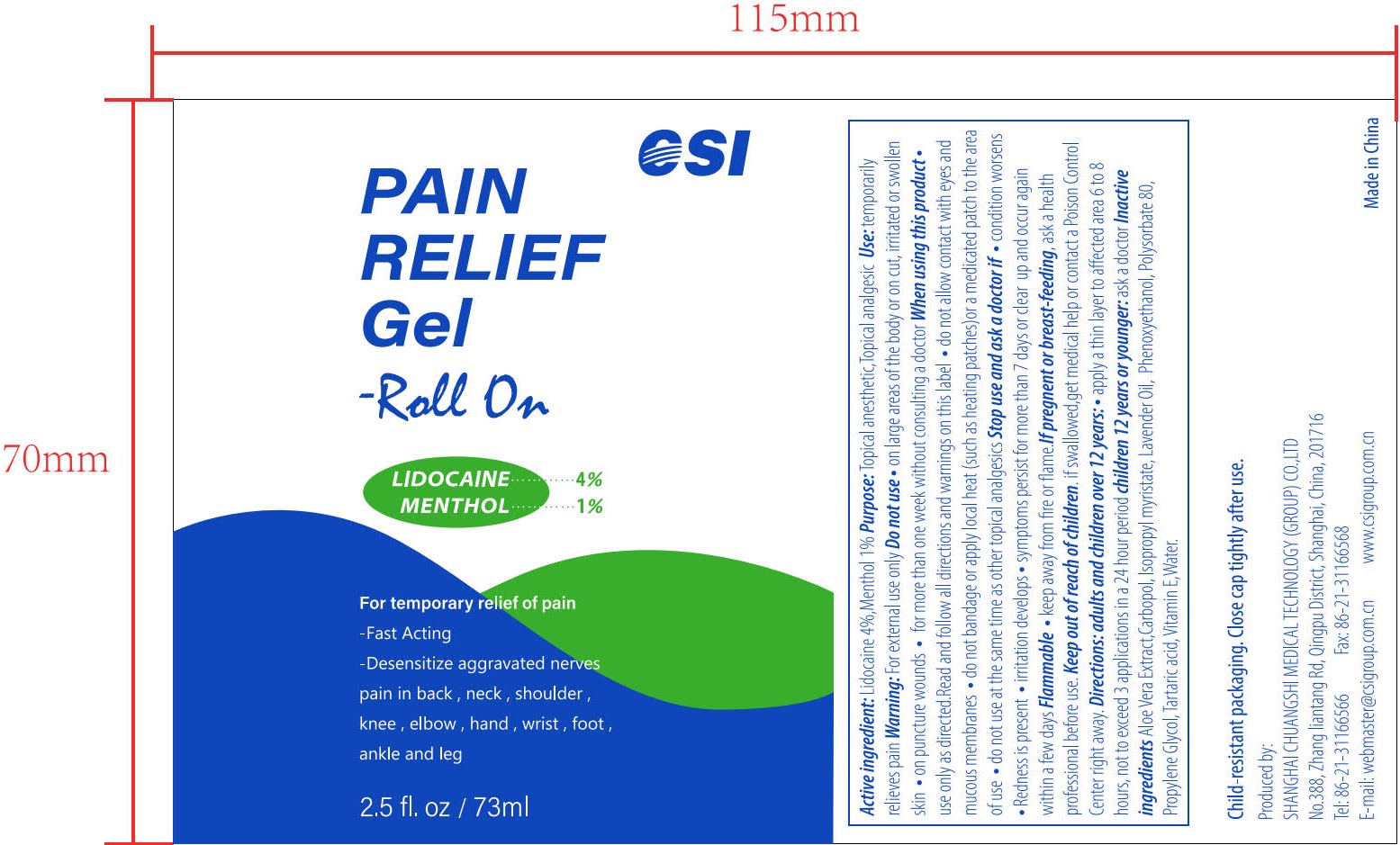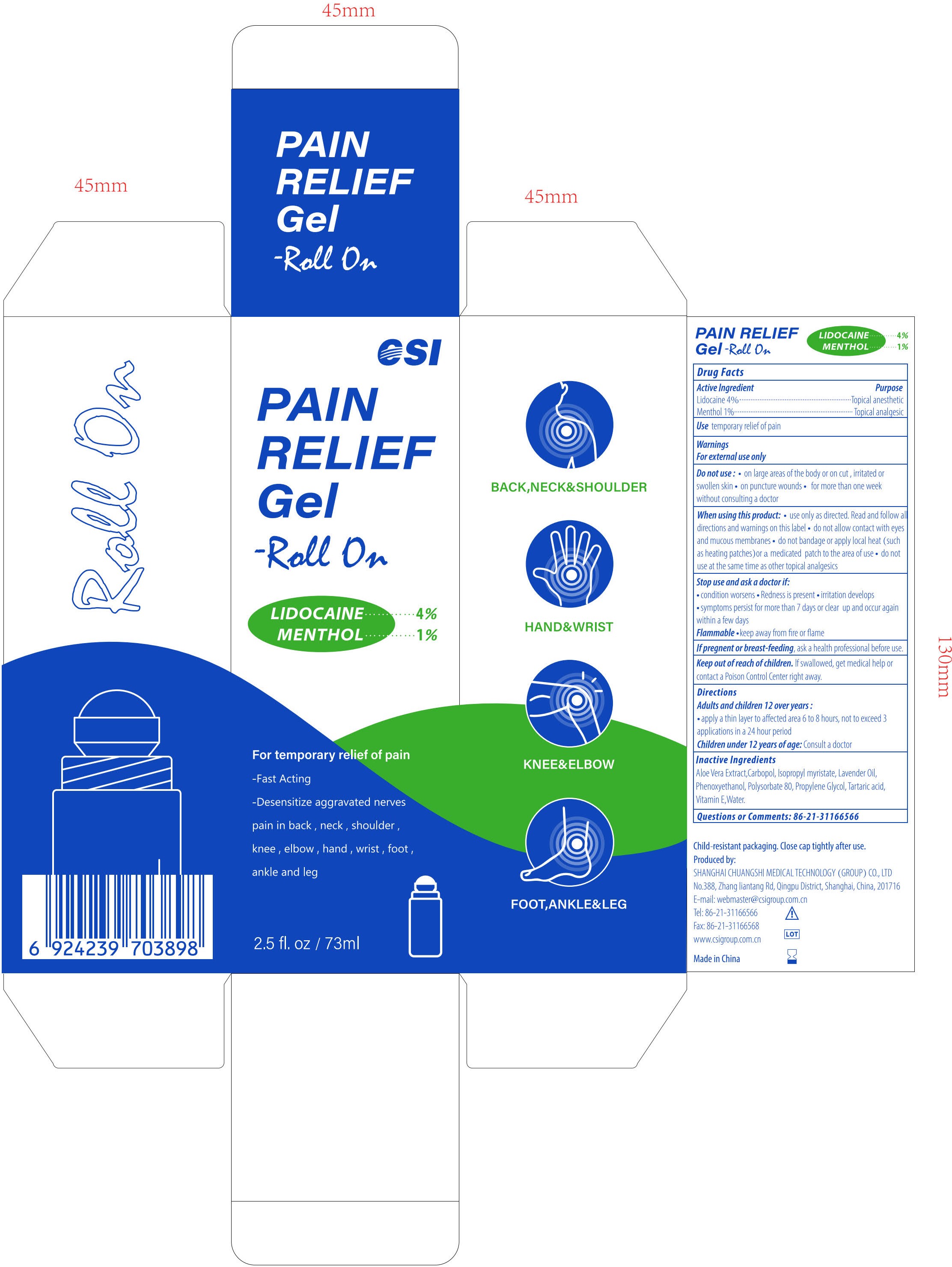 DRUG LABEL: PAIN RELIEF Gel-Roll On
NDC: 73557-373 | Form: GEL
Manufacturer: Shanghai Chuangshi Medical Technology (Group) Co., Ltd.
Category: otc | Type: HUMAN OTC DRUG LABEL
Date: 20241011

ACTIVE INGREDIENTS: LIDOCAINE 0.04 g/1 mL; MENTHOL 0.01 g/1 mL
INACTIVE INGREDIENTS: POLYACRYLIC ACID (250000 MW); WATER; LAVENDER OIL; PHENOXYETHANOL; ISOPROPYL MYRISTATE; .ALPHA.-TOCOPHEROL, D-; ALOE VERA LEAF; PROPYLENE GLYCOL; TARTARIC ACID; POLYSORBATE 80

CSI, Lidocaine and Menthol, PAIN RELIEF Gel-Roll On, 2.5 fl. oz / 73 mL, Gel, Bottle

Active Ingredient

Lidocaine 4.0% (w/w ...... Purpose: Topical Anesthetic)

Menthol 1.0% (w/w ...... Purpose: Topical Analgesic)

Purpose

(Lidocaine) Topical Anesthetic

(Menthol) Topical Analgesic

Use

temporary relief of pain

Warnings

For external use only

Do not use

• on large areas of the body or on cut, irritated or swollen skin not apply to wounds or damaged skin • on puncture wounds • for more than one week without consulting a doctor

When using this product

• use only as directed. Read and follow all directions and warnings on this label • do not allow contact with eyes and mucous membranes • do not bandage or apply local heat (such as heating patches) or a medicated patch to the area of use • do not use at the same time as other topical analgesics

Stop use if

• condition worsens • redness is present • irritation develops • symptoms persist for more than 7 days or clear up and occur within a few days

Ask a doctor if

• condition worsens • redness is present • irritation develops • symptoms persist for more than 7 days or clear up and occur within a few days

Flammable

• keep away from fire or flame

If pregnant or breast-feeding

Ask a health professional before use

Keep out of reach of children

If swallowed, get medical help or contact a Poison Control Center right away

Directions

Adults and children 12 over years:

• apply a thin layer to affected area 6 to 8 hours, not to exceed 3 application in a 24 hour period

Children under 12 years of age: Consult a doctor

Inactive Ingredients

Aloe Vera Extract, Carbopol, Isopropyl myristate, Lavender Oil, Phenoxyethanol, Polysorbate 80, Propylene Glycol, Tartaric acid, Vitamin E, Water

Questions or Comments

86-21-31166566

GENERAL PRECAUTIONS

Child-resistant packaging. Close cap tightly after use.